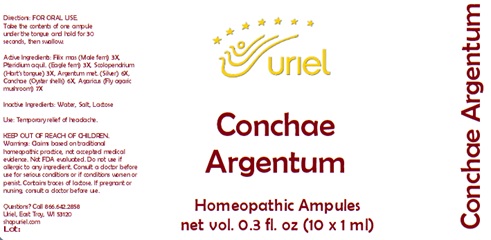 DRUG LABEL: Conchae Argentum
NDC: 48951-3117 | Form: LIQUID
Manufacturer: Uriel Pharmacy Inc.
Category: homeopathic | Type: HUMAN OTC DRUG LABEL
Date: 20231103

ACTIVE INGREDIENTS: DRYOPTERIS FILIX-MAS ROOT 3 [hp_X]/1 mL; PTERIDIUM AQUILINUM WHOLE 3 [hp_X]/1 mL; ASPLENIUM SCOLOPENDRIUM WHOLE 3 [hp_X]/1 mL; SILVER 6 [hp_X]/1 mL; OSTREA EDULIS SHELL 6 [hp_X]/1 mL; AMANITA MUSCARIA FRUITING BODY 7 [hp_X]/1 mL
INACTIVE INGREDIENTS: WATER; SODIUM CHLORIDE; LACTOSE

Conchae Argentum

INDICATIONS AND USAGE

Directions: FOR ORAL USE.

DOSAGE AND ADMINISTRATION

Take the contents of one ampule under the tongue and hold for 30 seconds, then swallow.

ACTIVE INGREDIENT

Active Ingredients: Filix mas (Male fern) 3X, Pteridium aquil. (Eagle fern) 3X, Scolopendrium (Hart’s tongue) 3X, Argentum met. (Silver) 6X,
Conchae (Oyster shells) 6X, Agaricus (Fly agaric mushroom) 7X

Inactive Ingredients: Water, Salt, Lactose

PURPOSE

Use: Temporary relief of headache.

KEEP OUT OF REACH OF CHILDREN.

WARNINGS

Warnings: Claims based on traditional homeopathic practice, not accepted medical evidence. Not FDA evaluated. Do not use if allergic to any ingredient. Consult a doctor before use for serious conditions or if conditions worsen or persist. Contains traces of lactose. If pregnant or nursing, consult a doctor before use.

Questions? Call 866.642.2858
Uriel, East Troy, WI 53120
shopuriel.com Lot: